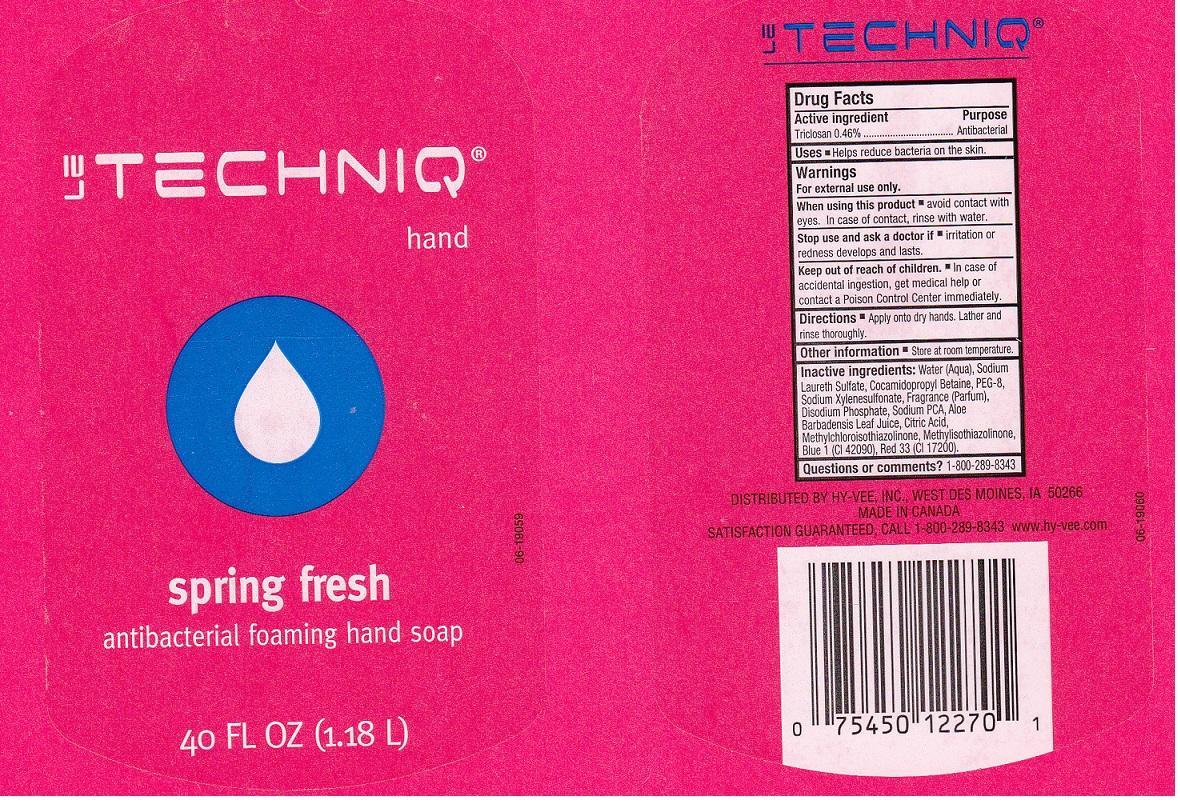 DRUG LABEL: LE TECHNIQ
NDC: 42507-100 | Form: LIQUID
Manufacturer: HYVEE INC
Category: otc | Type: HUMAN OTC DRUG LABEL
Date: 20130923

ACTIVE INGREDIENTS: TRICLOSAN 4.6 mg/1 mL
INACTIVE INGREDIENTS: WATER; SODIUM LAURETH SULFATE; COCAMIDOPROPYL BETAINE; POLYETHYLENE GLYCOL 400; SODIUM XYLENESULFONATE; SODIUM PHOSPHATE, DIBASIC ANHYDROUS; SODIUM PYRROLIDONE CARBOXYLATE; ALOE VERA LEAF; CITRIC ACID MONOHYDRATE; METHYLCHLOROISOTHIAZOLINONE; METHYLISOTHIAZOLINONE; FD&C BLUE NO. 1; D&C RED NO. 33

DRUG FACTS

ACTIVE INGREDIENT

TRICLOSAN 0.46%

PURPOSE

ANTIBACTERIAL

USES

HELPS REDUCE BACTERIA ON THE SKIN.

WARNINGS

FOR EXTERNAL USE ONLY.

WHEN USING THIS PRODUCT

AVOID CONTACT WITH EYES. IN CASE OF CONTACT, RINSE WITH WATER.

STOP USE AND ASK A DOCTOR IF

IRRITATION OR REDNESS DEVELOPS AND LASTS.

KEEP OUT OF REACH OF CHILDREN

IN CASE OF ACCIDENTAL INGESTION, GET MEDICAL HELP OR CONTACT A POISON CONTROL CENTER IMMEDIATELY.

DIRECTIONS

APPLY ONTO DRY HANDS. LATHER AND RINSE THOROUGHLY.

OTHER INFORMATION

STORE AT ROOM TEMPERATURE.

INACTIVE INGREDIENTS:

WATER (AQUA), SODIUM LAURETH SULFATE, COCAMIDOPROPYL BETAINE, PEG-8, SODIUM XYLENESULFONATE, FRAGRANCE (PARFUM), DISODIUM PHOSHATE, SODIUM PCA, ALOE BARBADENSIS LEAF JUICE, CITRIC ACID, METHYLCHLOROISOTHIAZOLINONE, METHYLISOTHIAZONLINONE, BLUE 1 (CI 42090), RED 33 (CI 17200).

QUESTIONS OR COMMENTS?

1-800-289-8343